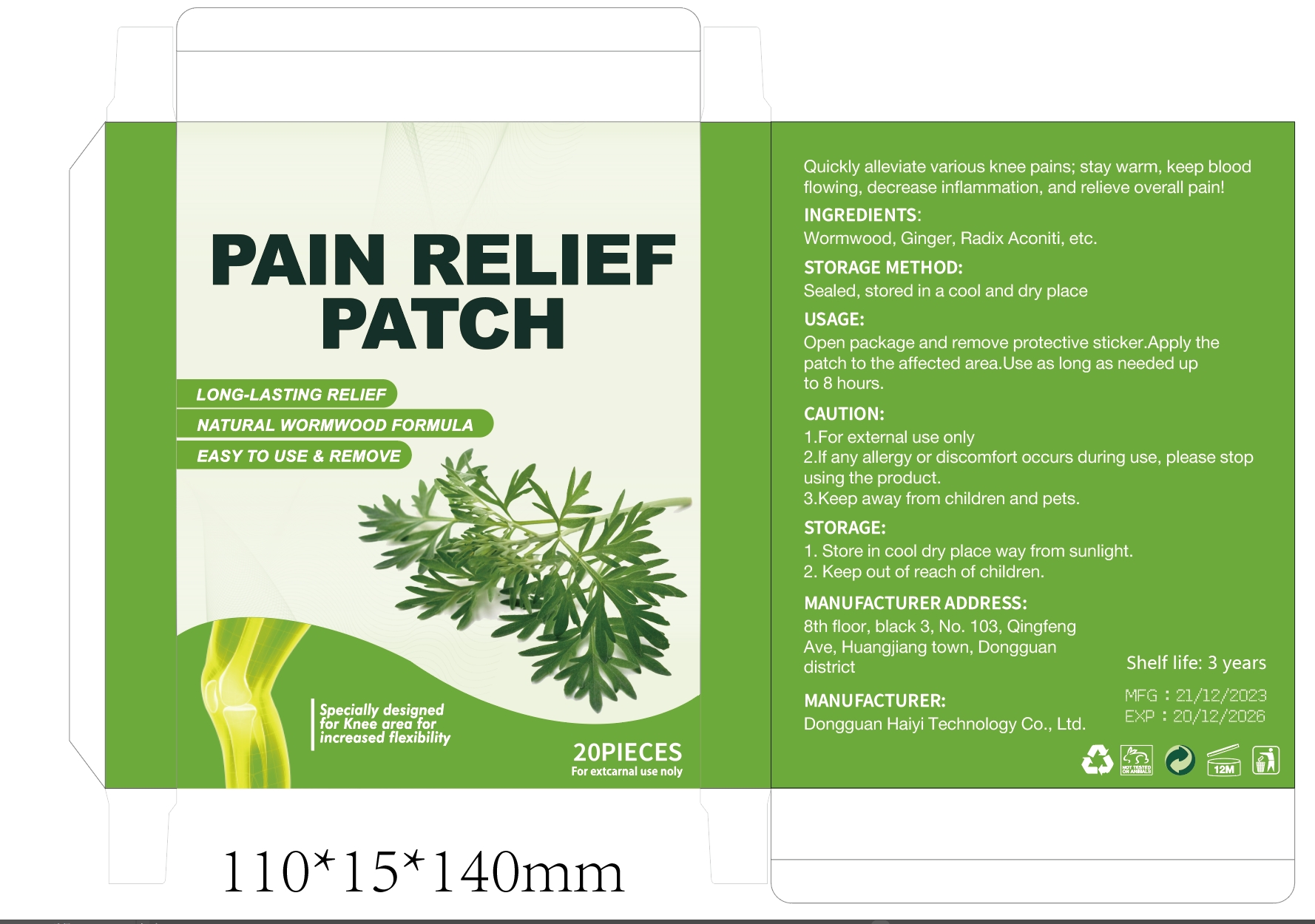 DRUG LABEL: PAIN RELIEF Patch
NDC: 84732-093 | Form: PATCH
Manufacturer: Dongguan Haiyi Technology Co.,Ltd.
Category: otc | Type: HUMAN OTC DRUG LABEL
Date: 20241118

ACTIVE INGREDIENTS: GINGER 1 mg/100 g
INACTIVE INGREDIENTS: WORMWOOD; ACONITUM NAPELLUS ROOT

Active ingredient

Ginger

Inactive ingredient

Wormwood, Radix Aconiti

Purpose section

Quickly all eviate various knee pains; stay warm, keep blood flowing, decrease inflammation, and relieve over all pain!

Warning

1.For external use onlyusing the product.
2.lf any allergy or discomfort occurs during use, please stop

3.Keep away from children and pets.

stop use

This product may cause allergic reactions in asmall number of people.
lf you experience any discomfort,please stop using it immediately.

not use

Not suitable for use by children, pregnantor breast feeding people.

OUT OF CHILDREN

KEEP THE PRODUCT OUT OF REACH OF CHILDREN to

HOW TO USE

Open package and remove protective sticker.

Apply the patch to the affected area.

Use as long as needed upto 8 hours.

Dosage

take an appropriateamount,Use 2-3 times a week